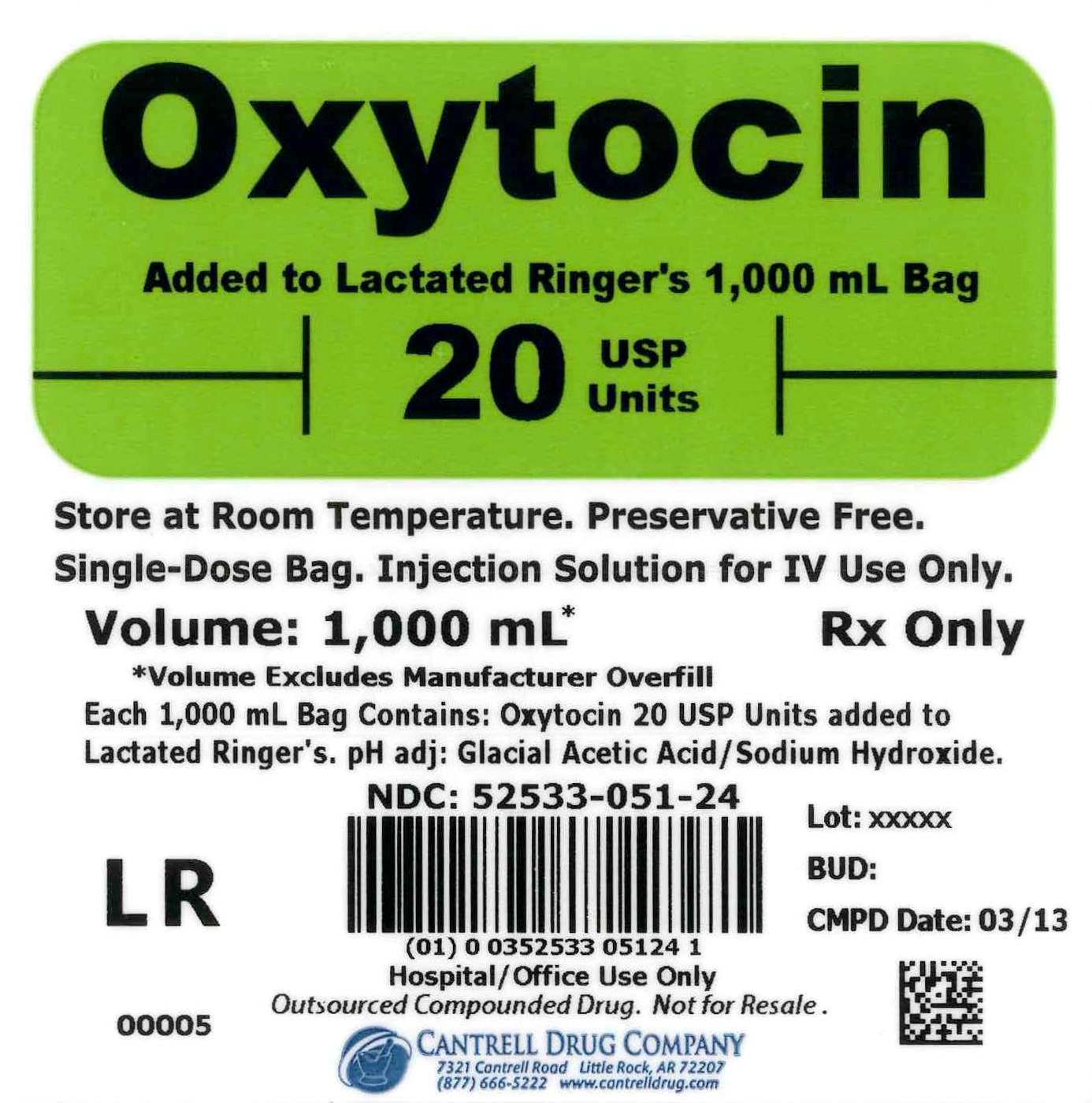 DRUG LABEL: Oxytocin
NDC: 52533-051 | Form: INJECTION, SOLUTION
Manufacturer: Cantrell Drug Company
Category: prescription | Type: HUMAN PRESCRIPTION DRUG LABEL
Date: 20150116

ACTIVE INGREDIENTS: OXYTOCIN 2 [USP'U]/100 mL
INACTIVE INGREDIENTS: WATER; SODIUM CHLORIDE 600 mg/100 mL; SODIUM LACTATE 310 mg/100 mL; POTASSIUM CHLORIDE 30 mg/100 mL; CALCIUM CHLORIDE 20 mg/100 mL

Oxytocin 20 USP Units Added to Lactated Ringer's 1,000 mL Bag